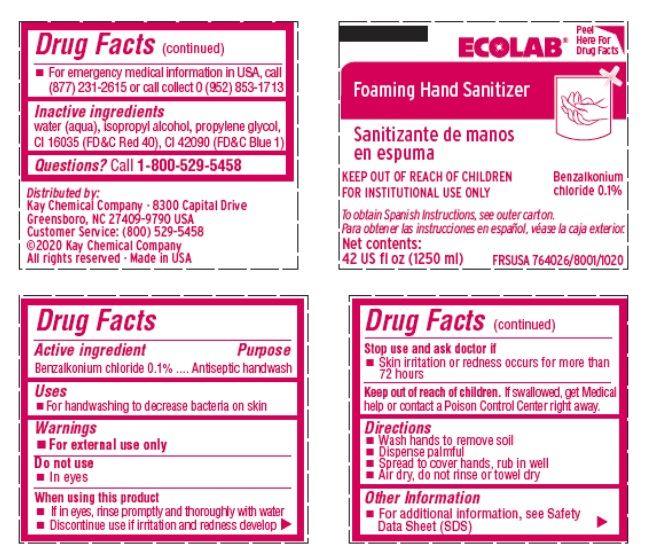 DRUG LABEL: Ecolab Foaming Hand Sanitizer
NDC: 47593-677 | Form: SOLUTION
Manufacturer: Ecolab Inc.
Category: otc | Type: HUMAN OTC DRUG LABEL
Date: 20251231

ACTIVE INGREDIENTS: BENZALKONIUM CHLORIDE 1 mg/1 mL
INACTIVE INGREDIENTS: WATER; ISOPROPYL ALCOHOL; PROPYLENE GLYCOL; FD&C RED NO. 40; FD&C BLUE NO. 1

Drug Facts

Active ingredient

Benzalkonium chloride 0.1%

Purpose

Antiseptic handwash

Uses

- For handwashing to decrease bacteria on the skin

Warnings

For external use only

Do not use

- In eyes

When using this product

- If in eyes, rinse promptly and thoroughly with water
- Discontinue use if irritation and redness develop

Stop use and ask a doctor if

- Skin irritation and redness occurs for more than 72 hours

Keep out of reach of children. If swallowed, get medical help or contact a Poison Control Center right away.

Directions

- Wash hands to remove soil
- Dispense palmful
- Spread to cover hands, rub in well
- Air dry, do not rinse or towel dry

Other Information

- for additional information, see Material Safety Data Sheet (MSDS)
- For emergency medical information in USA, call (877) 231-2615 or call collect 0 (952) 853-1713

INACTIVE INGREDIENT

Inactive ingredients water (aqua), isopropyl alcohol, propylene glycol, CI 16035 (FD&C Red 40), CI 42090 (FD&C Blue 1)

Questions? Call 1-800-529-5458

Principal display panel and representative container

Ecolab Foaming Hand Sanitizer

KEEP OUT OF REACH OF CHILDREN

FOR INSTITUTIONAL USE ONLY

Benzalkonium chloride 0.1%

Net Contents:

42 US fl oz (1250 ml)

FRSUSA 764026/8001/1020

Distributed by:

Kay Chemical Company · 8300 Capital Drive

Greensboro, NC 27409-9790 USA Customer Service: (800) 529-5458

©2020 Kay Chemical Company

All rights reserved · Made in USA